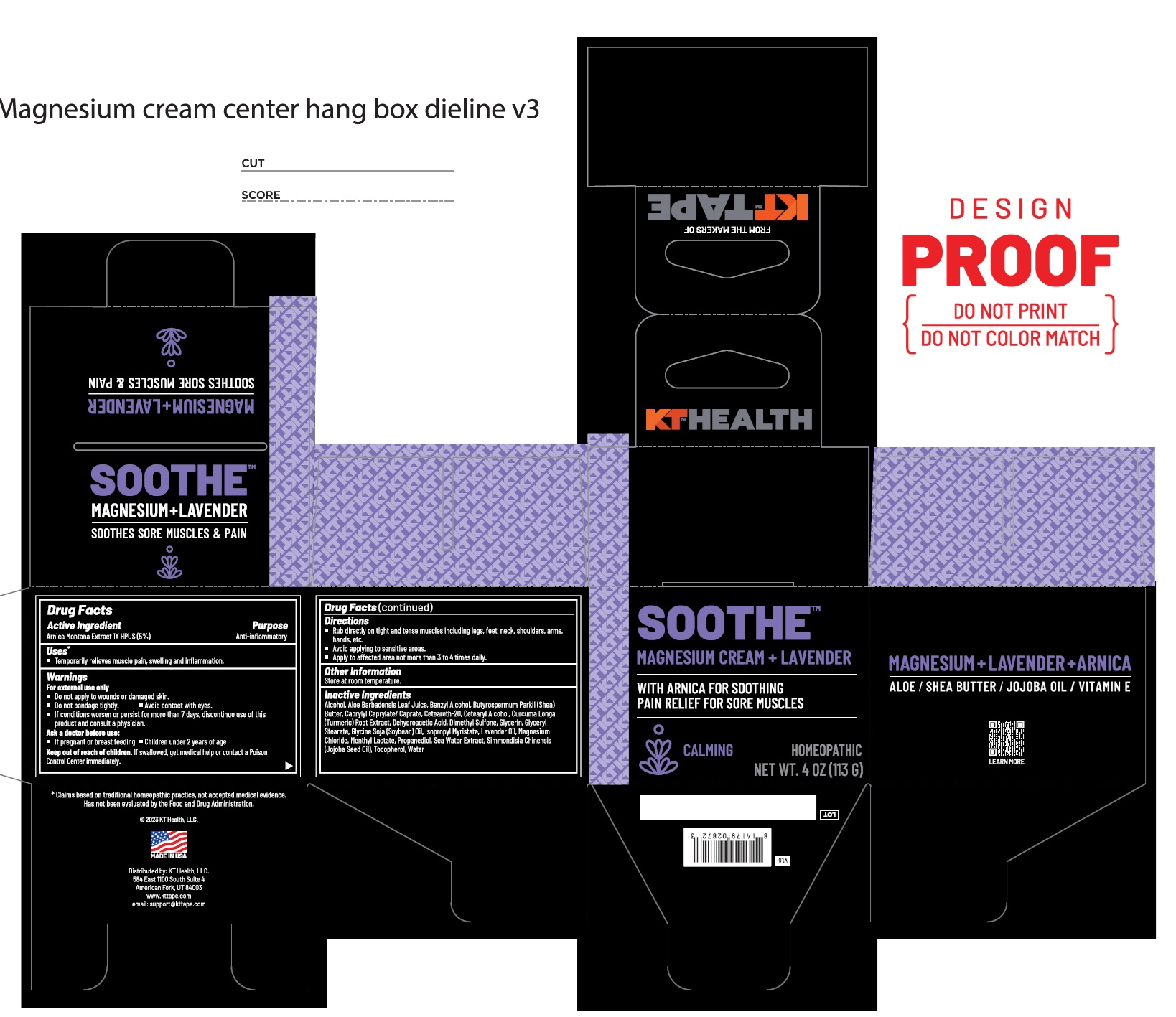 DRUG LABEL: KT HELATH SOOTHE MAGNESIUM, LAVENDER
NDC: 73044-106 | Form: CREAM
Manufacturer: KT Health LLC
Category: homeopathic | Type: HUMAN OTC DRUG LABEL
Date: 20250210

ACTIVE INGREDIENTS: ARNICA MONTANA WHOLE 5 g/100 g
INACTIVE INGREDIENTS: ALOE VERA FLOWER; ALCOHOL; EGMOL; SHEA BUTTER; CAPRYLYL CAPRYLATE/CAPRATE; CETOSTEARYL ALCOHOL; POLYOXYL 20 CETOSTEARYL ETHER; TURMERONE, AR-(+/-)-; DEHYDROACETIC ACID; GLYCERIN; GLYCERYL MONOSTEARATE; SOYBEAN OIL; MAGNESIUM CHLORIDE; MENTHYL ETHYLENE GLYCOL CARBONATE, (-)-; ISOPROPYL MYRISTATE; PROPANEDIOL; JOJOBA OIL; TOCOPHEROL; DIMETHYL SULFONE; LAVENDER OIL; WATER

Active Ingredients Purpose

Arnica Montana Extract
1X HPUS (5%) Anti-inflammatory

Uses

- Temporarily relieves muscle pain, swelling and inflammation.

Warnings

For external use only

- Do not apply to wounds or damaged skin.
- Do not bandage tightly. Avoid contact with eyes.
- If conditions worsen or persist for more than 7 days, discontinue use of this product and consult a physician.

Ask a doctor before use:

- If pregnant or breast feeding
- Children under 2 years of age

Keep out of reach of children. If swallowed, get medical help or contact a Poison Control Center immediately.

Directions

- Rub directly on tight and tense muscles including legs, feet, neck, shoulders, arms, hands, etc.
- Avoid applying to sensitive areas.
- Apply to affected area not more than 3 to 4 times daily.

Inactive Ingredients

Aloe Barbadensis Leaf Juice, Alcohol, Benzyl Alcohol, Butyrospermum Parkii (Shea) Butter, Caprylyl Caprylate/Caprate,Cetearyl Alcohol, Ceteareth-20, Curcuma Longa (Turmeric) Root Extract, Dehydroacetic Acid, Glycerin, Glyceryl Stearate, Glycine Soja (Soybean) Oil, Lavendar Oil , Magnesium Chloride, Menthyl Lactate, Isopropyl Myristate, Sea Water Extract, Propanediol,Simmondisia Chinensis (Jojoba Seed Oil), Tocopherol, Water

Other Information

Store at room temperature.